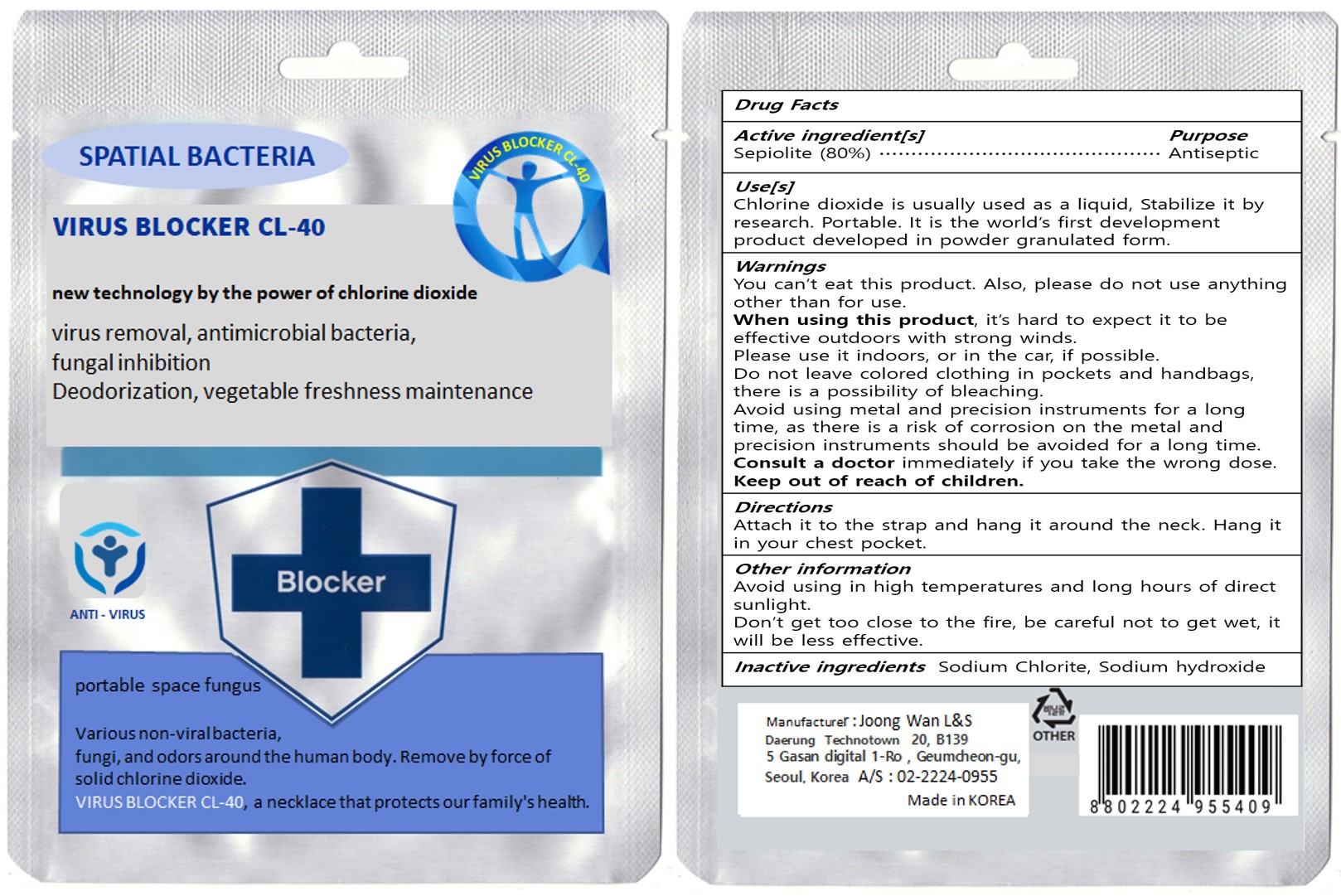 DRUG LABEL: VIRUS BLOCKER CL-40
NDC: 80965-201 | Form: STICK
Manufacturer: JOONGWAN LIFE & STYLE Co.ltd
Category: otc | Type: HUMAN OTC DRUG LABEL
Date: 20201030

ACTIVE INGREDIENTS: MAGNESIUM TRISILICATE 80 g/100 g
INACTIVE INGREDIENTS: SODIUM HYDROXIDE; SODIUM CHLORITE

80965-201

Active ingredient

Sepiolite (80%)

Purpose

Antiseptic

Use

Chlorine dioxide is usually used as a liquid, Stabilize it by research. Portable. It is the world’s first development product developed in powder granulated form.

Warnings

You can’t eat this product. Also, please do not use anything other than for use.

When using this product,

it’s hard to expect it to be effective outdoors with strong winds.

Please use it indoors, or in the car, if possible.

Do not leave colored clothing in pockets and handbags, there is a possibility of bleaching.

Avoid using metal and precision instruments for a long time, as there is a risk of corrosion on the metal and precision instruments should be avoided for a long time.

Consult a doctor

immediately if you take the wrong dose.

Directions

Attach it to the strap and hang it around the neck. Hang it in your chest pocket.

Other information

Avoid using in high temperatures and long hours of direct sunlight.

Don’t get too close to the fire, be careful not to get wet, it will be less effective.

Inactive ingredients

Sodium Chlorite, Sodium hydroxide